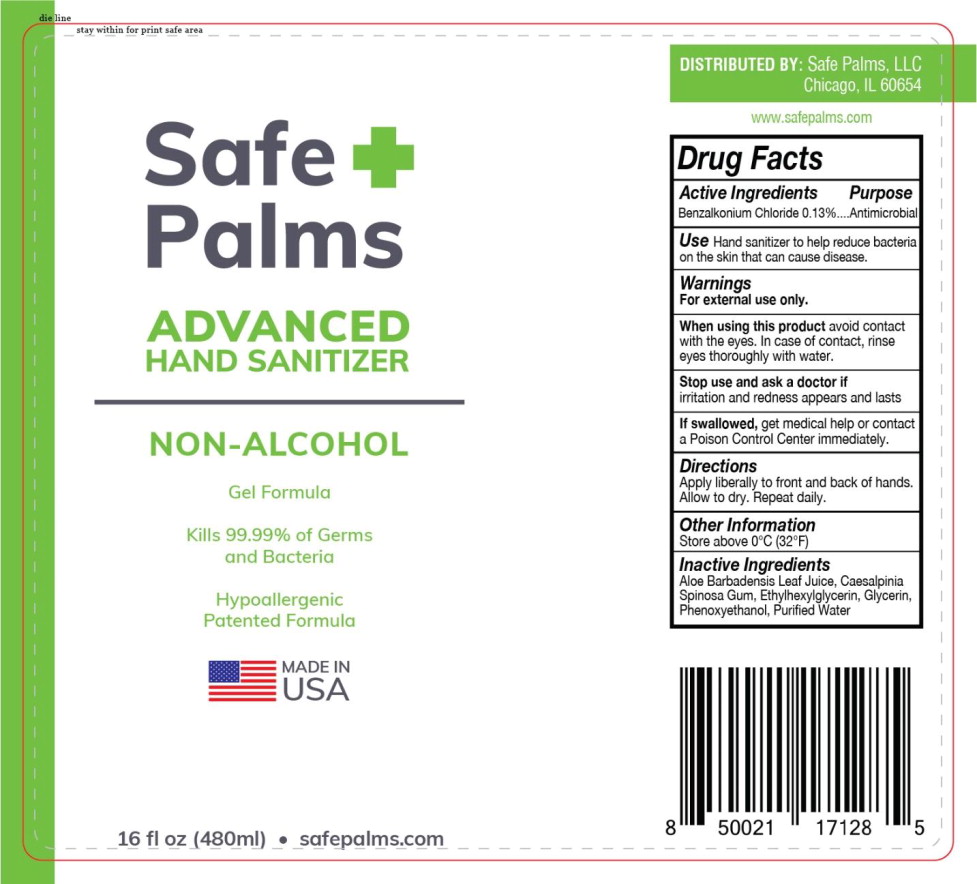 DRUG LABEL: Advanced Hand Sanitizer
NDC: 90117-201 | Form: GEL
Manufacturer: Safe Palms, LLC
Category: otc | Type: HUMAN OTC DRUG LABEL
Date: 20200825

ACTIVE INGREDIENTS: BENZALKONIUM CHLORIDE 0.13 g/100 mL
INACTIVE INGREDIENTS: ALOE VERA LEAF; CAESALPINIA SPINOSA RESIN; ETHYLHEXYLGLYCERIN; GLYCERIN; PHENOXYETHANOL; WATER

Drug Facts

Active Ingredients

Benzalkonium Chloride 0.13%

Purpose

Antimicrobial

Use

Hand sanitizer to help reduce bacteria on the skin that can cause disease.

Warnings

For external use only.

When using this product avoid contact with the eyes. In case of contact, rinse eyes thoroughly with water.

Stop use and ask a doctor if irritation and redness appears and lasts

KEEP OUT OF REACH OF CHILDREN

If swallowed, get medical help or contact a Poison Control Center immediately.

Directions

Apply liberally to front and back of hands. Allow to dry. Repeat daily.

Other Information

Store above 0°C (32°F)

Inactive Ingredients

Aloe Barbadensis Leaf Juice, Caesalpinia Spinosa Gum, Ethylhexylglycerin, Glycerin, Phenoxyethanol, Purified Water

PACKAGE LABEL

Safe +
Palms

ADVANCED
HAND SANITIZER

NON-ALCOHOL

Gel Formula

Kills 99.99% of Germs
and Bacteria

Hypoallergenic
Patented Formula

MADE IN
USA

16 fl oz (480ml) • safepalms.com